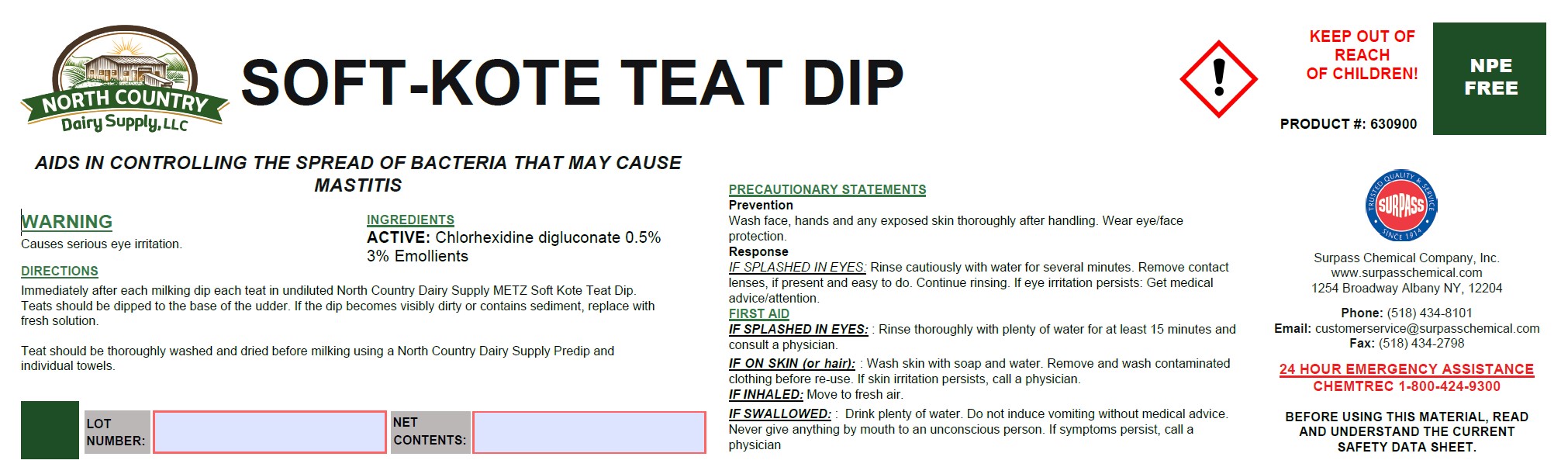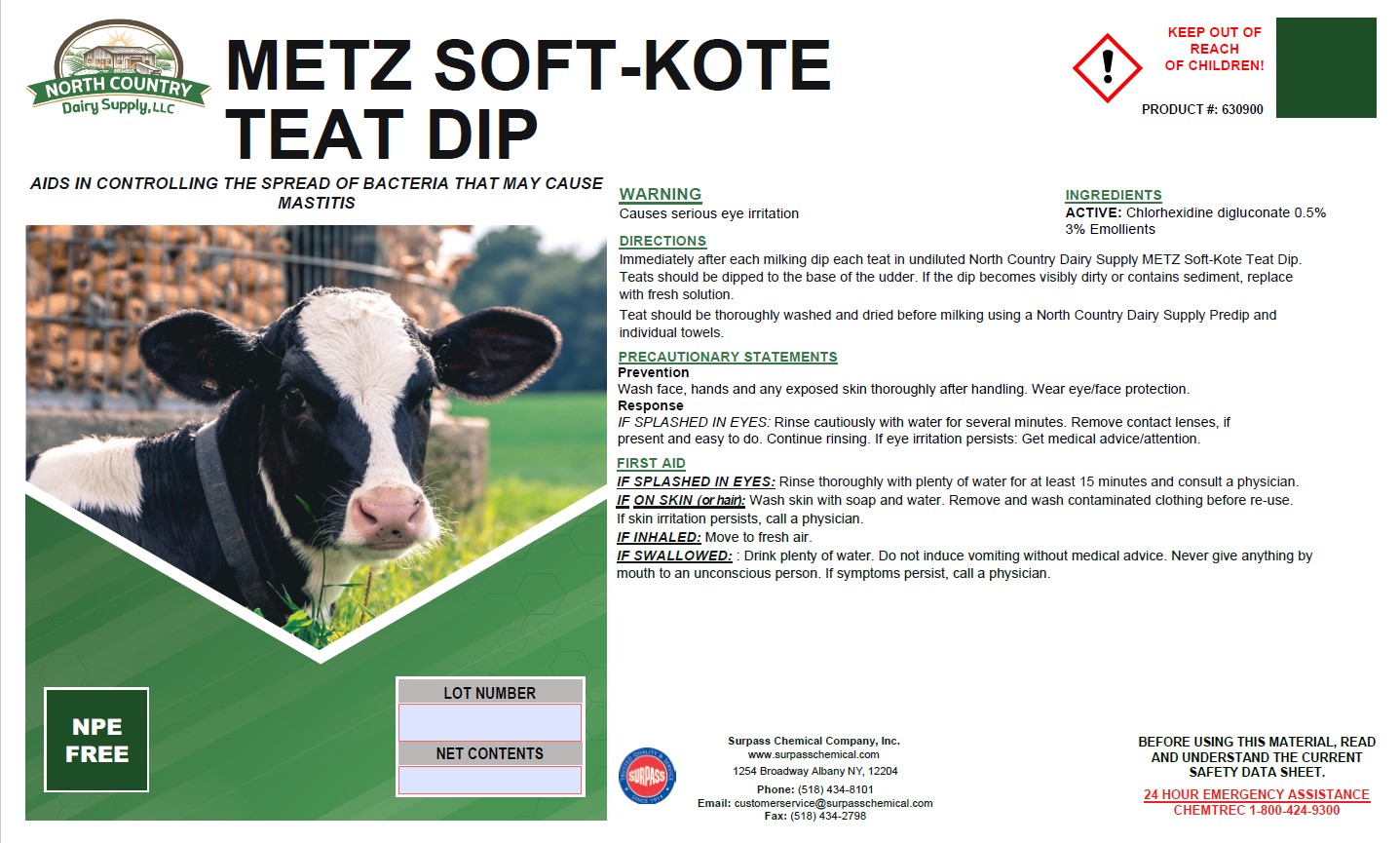 DRUG LABEL: Metz Soft Kote Teat Dip
NDC: 86067-0127 | Form: SOLUTION
Manufacturer: Surpass Chemical. Company, Inc.
Category: animal | Type: OTC ANIMAL DRUG LABEL
Date: 20251229

ACTIVE INGREDIENTS: CHLORHEXIDINE 0.005 kg/1 kg
INACTIVE INGREDIENTS: WATER 0.9517 kg/1 kg; HYDROXYETHYLCELLULOSE 0.003 kg/1 kg; C9-11 PARETH-3 0.01 kg/1 kg; GLYCERIN 0.03 kg/1 kg; FD&C BLUE NO. 1 0.0002 kg/1 kg; ANHYDROUS CITRIC ACID 0.0001 kg/1 kg

Metz Soft Kote Teat Dip

DESCRIPTION

METZ SOFT KOTE TEAT Dip

AIDS IN CONTROLLING THE SPREAD OF BACTERIA THAT MAY CAUSE MASTITIS PRODUCT #: 630900

WARNING
Causes serious eye irritation.

DIRECTIONS:

Immediately after each milking dip each teat in undiluted North Country Dairy Supply METZ Soft Kote Teat Dip. Teats should be dipped to the base of the udder. If the dip becomes visibly dirty or contains sediment, replace with fresh solution.
At the end of lactation, the teat should be dipped with North Country Dairy Supply METZ Soft Kote Teat Dip for four days after the last milking.
Teat should be thoroughly washed and dried before milking using a North Country Dairy Supply Predip and individual towels.

GENERAL PRECAUTIONS

PRECAUTIONARY STATEMENTS
Prevention

Wash face, hands and any exposed skin throughly after handling. Wear eye/face protection.

Response

If in eyes: Rinse cautiously with water for several minutes. Remove contact lenses, if present and easy to do. Continue rinising. If eye irritation persists, get medical attention.

ACTIVE INGREDIENT

INGREDIENTS:
ACTIVE: Chlorhexidine digluconate 0.5%

3% Emollients

OTHER SAFETY INFORMATION

FIRST AID:
IF SPLASHED IN EYES: Rinse thoroughly with plenty of water for at least 15 minutes and consult a physician.
IN CASE OF CONTACT: Wash skin with soap and water. Remove and wash contaminated clothing before re-use. If skin irritation persists, cal la physician.
IF INHALED: Move to fresh air.
IF SWALLOWED: Drink plenty of water. Do not induce vomiting without medical advice. Never give anything by mouth to an unconscious person. If symptons persist, call a physician.

SAFE HANDLING WARNING

BEFORE USING THIS MATERIAL, READ AND
UNDERSTAND THE CURRENT SAFETY DATA SHEET.

Surpass Chemical Company, Inc. Phone: (518) 434-8101 24 HOUR EMERGENCY ASSISTANCE:
www.surpasschemical.com Fax: (518) 434-2798 CHEMTREC 1-800-424-9300
1254 Broadway Albany NY, 12204 Email: customerservice@surpasschemical.com KEEP OUT OF REACH OF CHILDREN!

KEEP OUT OF REACH OF CHILDREN!